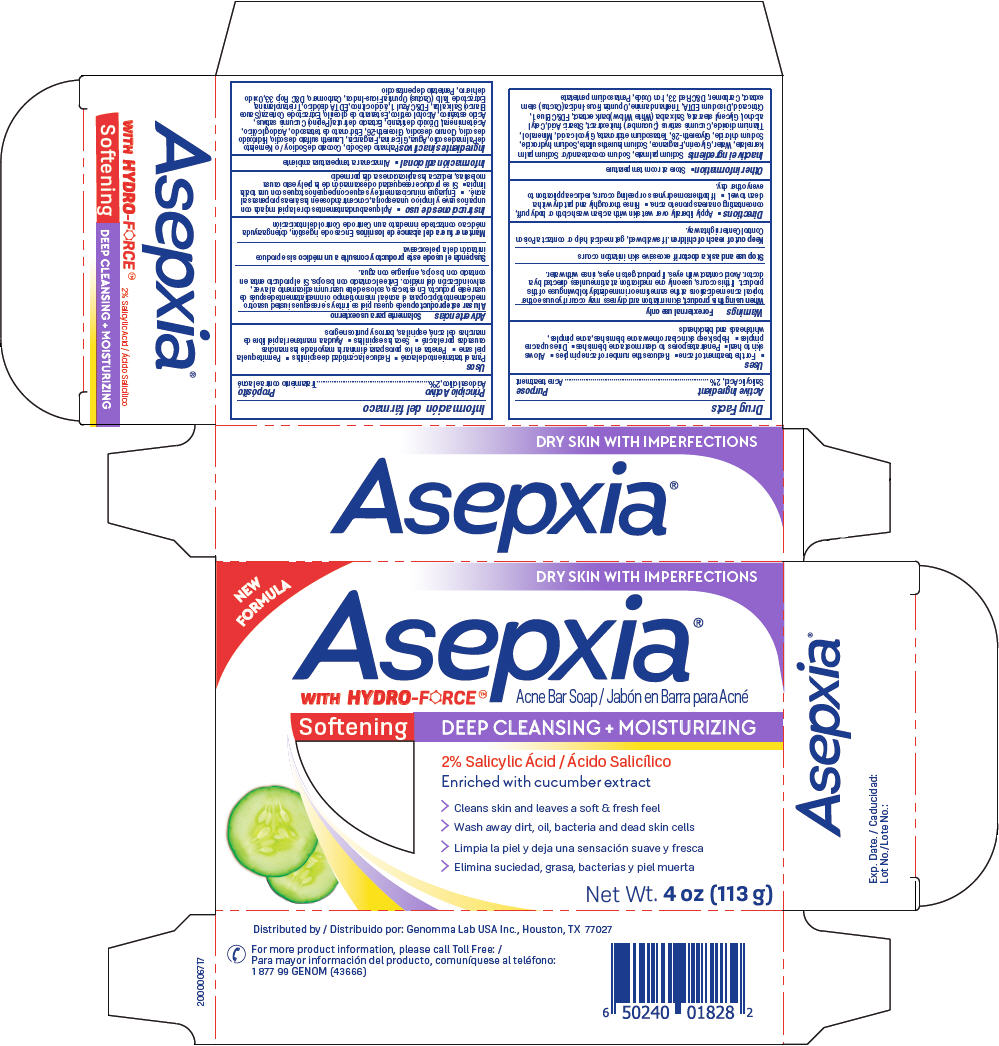 DRUG LABEL: Asepxia Softening Acne Bar
NDC: 50066-805 | Form: SOAP
Manufacturer: Genomma Lab USA
Category: otc | Type: HUMAN OTC DRUG LABEL
Date: 20231106

ACTIVE INGREDIENTS: SALICYLIC ACID 2 g/100 g
INACTIVE INGREDIENTS: GLYCOLIC ACID; MINERAL OIL; TITANIUM DIOXIDE; CUCUMBER; STEARIC ACID; CETYL ALCOHOL; GLYCERYL MONOSTEARATE; FD&C BLUE NO. 1; CITRIC ACID MONOHYDRATE; EDETATE DISODIUM ANHYDROUS; TROLAMINE; OPUNTIA FICUS-INDICA STEM; CARBOMER HOMOPOLYMER, UNSPECIFIED TYPE; D&C RED NO. 33; FERRIC OXIDE RED; PENTASODIUM PENTETATE; SODIUM PALMATE; SODIUM COCOATE; SODIUM PALM KERNELATE; WATER; GLYCERIN; SODIUM LAURETH-3 SULFATE; SODIUM HYDROXIDE; SODIUM CHLORIDE; GLYCERETH-26; ETIDRONATE TETRASODIUM

Asepxia Softening Acne Bar Soap®

Active Ingredient

Salicylic Acid, 2%

Purpose

Acne treatment

Uses

- For the treatment of acne
- Reduces the number of acne pimples
- Allows skin to heal
- Penetrates pores to clear most acne blemishes
- Dries up acne pimples
- Helps keep skin clear of new acne blemishes, acne pimples, whiteheads and blackheads

Warnings

For external use only

WHEN USING

, skin irritation and dryness may occur if you use other topical acne medications at the same time or immediately following use of this product. If this occurs, use only one medication at a time unless directed by a doctor. Avoid contact with eyes. If product gets in eyes, rinse with water. When using this product

STOP USE

excessive skin irritation occurs Stop use and ask a doctor if

KEEP OUT OF REACH OF CHILDREN

. If swallowed, get medical help or contact a Poison Control Center right away. Keep out of reach of children

Directions

- Apply liberally over wet skin with a clean wash cloth or body puff, concentrating on areas prone to acne.
- Rinse thoroughly and pat dry with a clean towel.
- If bothersome dryness or peeling occurs, reduce application to every other day.

Other information

- Store at room temperature

Inactive ingredients

Sodium palmate, Sodium cocoate and/or Sodium palm kernelate, Water, Glycerin, Fragrance, Sodium laureth sulfate, Sodium hydroxide, Sodium chloride, Glycereth-26, Tetrasodium etidronate, Glycolic acid, Mineral oil, Titanium dioxide, Cucumis sativus (Cucumber) fruit extract, Stearic Acid, Cetyl alcohol, Glyceryl stearate, Salix alba (White Willow) bark extract, FD&C Blue 1, Citric acid, Disodium EDTA, Triethanolamine, Opuntia Ficus-Indica (Cactus) stem extract, Carbomer, D&C Red 33, Iron Oxide, Pentasodium pentetate

QUESTIONS

For more product information, please call Toll Free: 1 877 99 GENOM (43666)

Distributed by: Genomma Lab USA Inc., Houston, TX 77027

PRINCIPAL DISPLAY PANEL - 113 g Bar Carton

NEW FORMULA

DRY SKIN WITH IMPERFECTIONS

Acne Bar Soap Asepxia WITH HYDRO-FORCE®®

Softening DEEP CLEANSING + MOISTURIZING

2% Salicylic Ácid

Enriched with cucumber extract

> Cleans skin and leaves a soft & fresh feel

> Wash away dirt, oil, bacteria and dead skin cells

Net Wt. 4 oz (113 g)